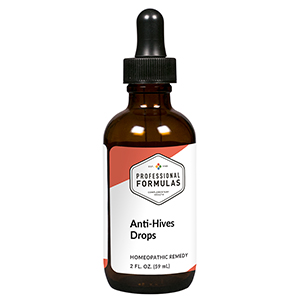 DRUG LABEL: Anti-Hives Drops
NDC: 63083-2004 | Form: LIQUID
Manufacturer: Professional Complementary Health Formulas
Category: homeopathic | Type: HUMAN OTC DRUG LABEL
Date: 20190815

ACTIVE INGREDIENTS: PANTOTHENIC ACID 2 [hp_X]/59 mL; ASCORBIC ACID 3 [hp_X]/59 mL; EPINEPHRINE 6 [hp_X]/59 mL; MAGNESIUM PHOSPHATE, DIBASIC TRIHYDRATE 6 [hp_X]/59 mL; PYRIDOXINE 6 [hp_X]/59 mL; APIS MELLIFERA 6 [hp_X]/59 mL; BOS TAURUS LYMPH VESSEL 6 [hp_X]/59 mL; URTICA URENS WHOLE 6 [hp_X]/59 mL
INACTIVE INGREDIENTS: ALCOHOL; WATER

C4

ACTIVE INGREDIENTS

Pantothenic acid 2X
Ascorbic acid 3X
Adrenalinum 6X
Magnesia phosphorica 6X
Pyridoxine 6X
Apis mellifica 6X, 12X
Lymph 6X, 12X
Urtica urens 6X, 12X

QUESTIONS

Professional Formulas

PO Box 2034 Lake Oswego, OR 97035

INDICATIONS

For the temporary relief of itchy, raised, or colored welts on the skin.*

PURPOSE

*Claims based on traditional homeopathic practice, not accepted medical evidence. Not FDA evaluated.

WARNINGS

In case of overdose, get medical help or contact a poison control center right away.

Keep out of the reach of children.

PREGNANCY OR BREAST FEEDING

If pregnant or breastfeeding, ask a healthcare professional before use.

DIRECTIONS

Place drops under tongue 30 minutes before/after meals. Adults and children 12 years and over: Take 10 drops up to 3 times per day for up to 6 weeks. For immediate onset of symptoms, take 10 to 15 drops every 15 minutes up to 3 hours. For less severe symptoms, take 10-15 drops hourly up to 8 hours. Consult a physician for use in children under 12 years of age.

OTHER INFORMATION

Tamper resistant. If seal is broken, do not use. After opening, close container tightly and store at room temperature away from heat.

INACTIVE INGREDIENTS

20% ethanol, purified water.

LABEL

Est 1985

Professional Formulas

Complementary Health

Anti-Hives Drops

Homeopathic Remedy

2 FL. OZ. (59 mL)